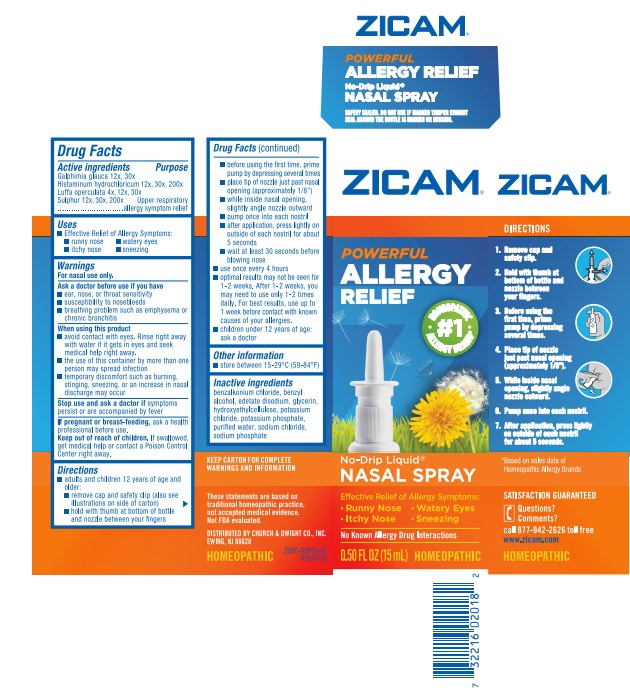 DRUG LABEL: Zicam Allergy Relief
NDC: 10237-463 | Form: SPRAY
Manufacturer: Church & Dwight Co., Inc.
Category: homeopathic | Type: HUMAN OTC DRUG LABEL
Date: 20241119

ACTIVE INGREDIENTS: GALPHIMIA GLAUCA FLOWERING TOP 30 [hp_X]/1 mL; HISTAMINE DIHYDROCHLORIDE 200 [hp_X]/1 mL; LUFFA OPERCULATA FRUIT 30 [hp_X]/1 mL; SULFUR 200 [hp_X]/1 mL
INACTIVE INGREDIENTS: BENZALKONIUM CHLORIDE; BENZYL ALCOHOL; EDETATE DISODIUM; GLYCERIN; HYDROXYETHYL CELLULOSE (100 MPA.S AT 2%); POTASSIUM CHLORIDE; POTASSIUM PHOSPHATE, UNSPECIFIED FORM; WATER; SODIUM CHLORIDE; SODIUM PHOSPHATE

Zicam®Allergy Relief Nasal Spray

Active Ingredients

Galphimia glauca 12x, 30x
Histaminum hydrochloricum 12x, 30x, 200x
Luffa operculata 4x, 12x, 30x
Sulphur 12x, 30x, 200x

Purpose

Upper respiratory allergy symptom relief

Uses

- Effective Relief of Allergy Symptoms:
  - runny nose
  - itchy nose
  - watery eyes
  - sneezing

Warnings

For nasal use only.

Ask a doctor before use if you have

- ear, nose, or throat sensitivity
- susceptibility to nosebleeds
- breathing problems such as emphysema or chronic bronchitis

When using this product

- avoid contact with eyes. Rinse right away with water if it gets in eyes and seek medical help right away.
- the use of this container by more than one person may spread infection
- teamporary discomfort such as burning, stinging, sneezing, or an increase in nasal discharge may occur

Stop use and ask a doctor ifsymptoms persist or are accompanied by fever

PREGNANCY OR BREAST FEEDING

If pregnant or breast-feeding,ask a health professional before use.

Keep out of reach of children.If swallowed, get medical help or contact a Poison Control Center right away.

Directions

- adults and children 12 years of age and older:
  - remove cap and safety clip (also see illustrations on side of carton)
  - hold with thumb at bottom of bottle and nozzle between your fingers
  - before using the first time, prime pump by depressing several times
  - place tip of nozzle just past nasal opening (approximately 1/8")
  - while inside nasal opening, slightly angle nozzle outward
  - pump once into each nostril
  - after application, press lightly on outside of each nostril for about 5 seconds
  - wait at least 30 seconds before blowing nose
- use once every 4 hours
- optimal results may not be seen for 1-2 weeks. After 1-2 weeks, you may need to use only 1-2 times daily. For best results, use up to 1 week before contact with known causes of your allergies.
- children under 12 years of age: ask a doctor

Other information

- store between 15-29°C (59-84°F)

Inactive ingredients

benzalkonium chloride, benzyl alcohol, edetate disodium, glycerin, hydroxyethylcellulose, potassium chloride, potassium phosphate, purified water, sodium chloride, sodium phosphate

Questions? Comments?

call 877-942-2626 toll free

www.zicam.com

PRINCIPAL DISPLAY PANEL - 15 mL Bottle Carton

ZICAM®

POWERFUL
ALLERGY
RELIEF

HOMEOPATHIC
• #1•
ALLERGY BRAND*

No-Drip Liquid®
NASAL SPRAY

Effective Relief of Allergy Symptoms:

- Runny Nose
- Watery Eyes
- Itchy Nose
- Sneezing

No Known Allergy Drug Interactions

0.50 FL OZ (15 mL)
HOMEOPATHIC